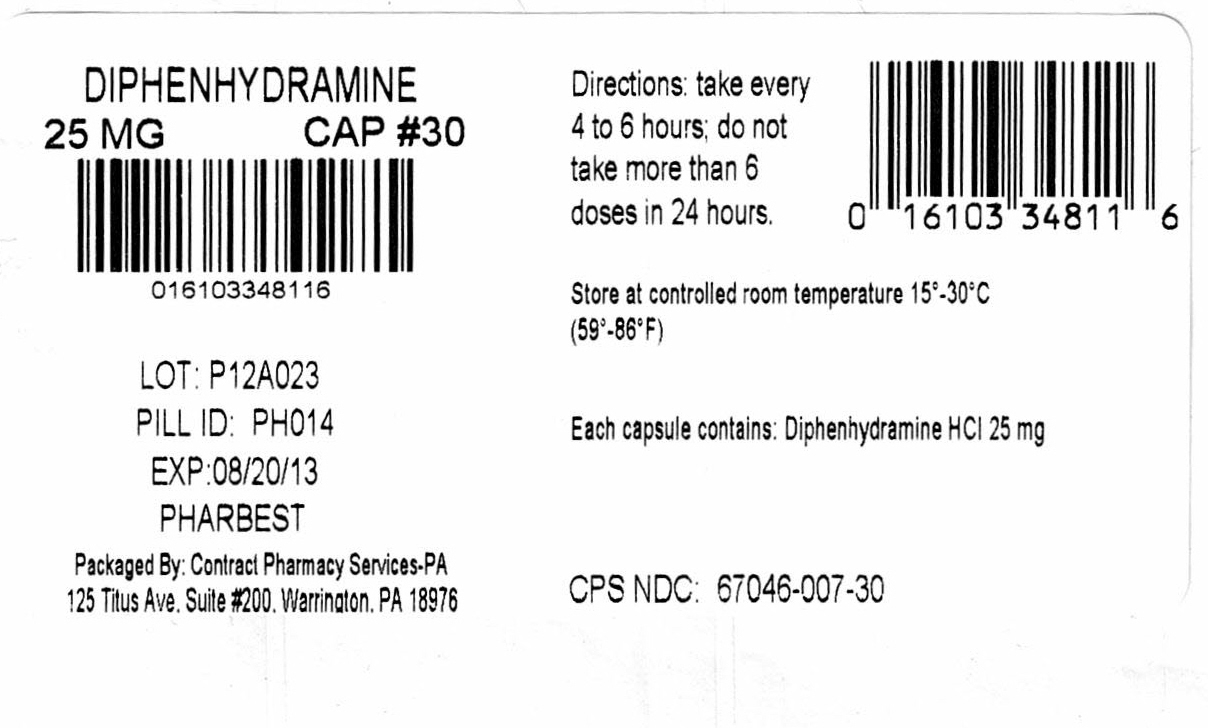 DRUG LABEL: Pharbedryl
NDC: 67046-007 | Form: CAPSULE
Manufacturer: Contract Pharmacy Services-PA
Category: otc | Type: HUMAN OTC DRUG LABEL
Date: 20170911

ACTIVE INGREDIENTS: DIPHENHYDRAMINE HYDROCHLORIDE 25 mg/1 1
INACTIVE INGREDIENTS: FERROSOFERRIC OXIDE; D&C RED NO. 28; FD&C BLUE NO. 1; FD&C RED NO. 40; GELATIN; LACTOSE MONOHYDRATE; MAGNESIUM STEARATE; SILICON DIOXIDE; SODIUM LAURYL SULFATE

Diphenhydramine 25 mg Capsule #30 007
Drug Facts

Active ingredient(in each banded capsule)

Diphenhydramine HCL 25 mg

Purpose

Antihistamine

Uses:

Temporarily relieves these symptoms associated with the common cold, hay fever, or other respiratory allergies:

- Sneezing
- Nasal congestion
- Runny nose
- Itchy, watery eyes

Do not use

- With any other product containing diphenhydramine, even one used on skin.

Ask a doctor or pharmacist before use

If you have

- Trouble urinating due to an enlarged prostate gland
- A breathing problem such as emphysema or chronic bronchitis
- Glaucoma

Ask a doctor or pharmacist before use of you are

taking sedatives or tranquilizers

When using this product

- Avoid alcoholic drinks
- Marked drowsiness may occur
- Excitability may occur, especially in children
- Alcohol, sedatives and tranquilizers may increase drowsiness
- Be careful when driving a motor vehicle or operating machinery

If pregnant or breast-feeding,

ask a health professional before use.

Keep out of reach of children.

In case of accidental overdose, get medical help or contact a Poison Control Center immediately.

Directions:

- Take every 4-6 hours
- Do not exceed 6 doses in 24 hours.

Adults and children 12 years of age or over | 25 mg to 50 mg (1 to 2 capsules)
Children 6 to under 12 years of age | 12.5 mg** to 25 mg (1 capsule)
Children under 6 years | ask a doctor

**12.5 mg dosage strength is not available in this package.
Do not attempt to break capsule.

Other information:

- Tamper Evident: Do not use if safety seal under cap is broken or missing
- Store at controlled room temperature 15°-30°C (59°-86°F)
- Protect from moisture
- Use by expiration date on package

Questions? Adverse drug event call: (866)562-2756

Enter section text here